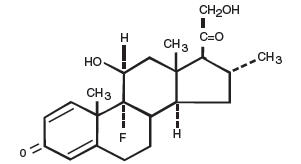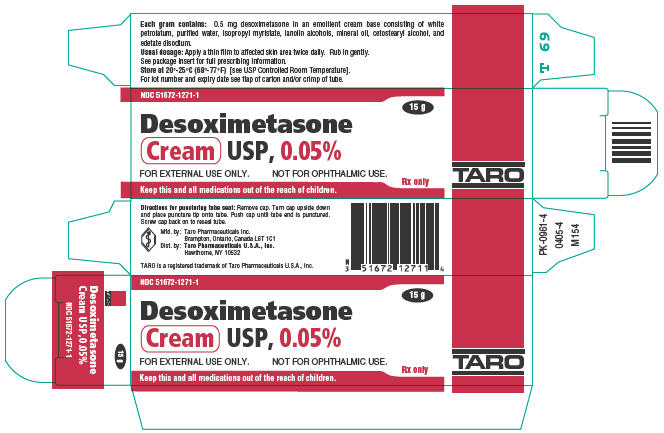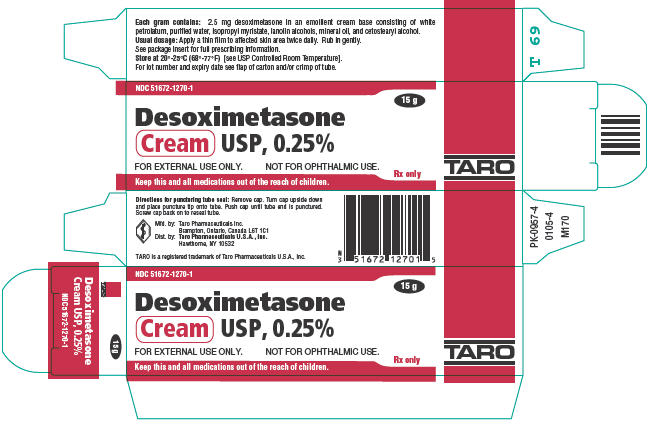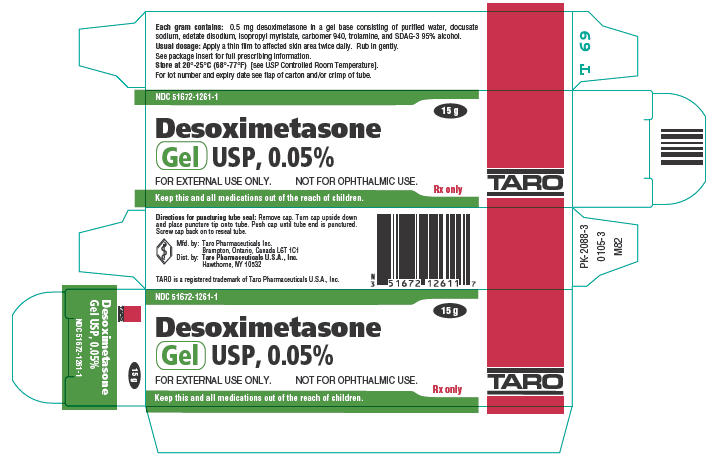 DRUG LABEL: Desoximetasone
NDC: 42254-015 | Form: CREAM
Manufacturer: Rebel Distributors Corp
Category: prescription | Type: HUMAN PRESCRIPTION DRUG LABEL
Date: 20111130

ACTIVE INGREDIENTS: desoximetasone 2.5 mg/1 g
INACTIVE INGREDIENTS: petrolatum; water; isopropyl myristate; mineral oil; cetostearyl alcohol

Desoximetasone
Cream USP, 0.05%, Cream USP, 0.25%
Gel USP, 0.05%

For external use only. Not for ophthalmic use.

Rx only

DESCRIPTION

Desoximetasone Cream USP, 0.05%; Desoximetasone Cream USP, 0.25% and Desoximetasone Gel USP, 0.05% contain desoximetasone a synthetic fluorinated corticosteroid for topical dermatologic use. The corticosteroids constitute a class of primarily synthetic steroids used topically as anti-inflammatory and anti-pruritic agents.

Chemically, desoximetasone is Pregna-1, 4-diene-3, 20-dione, 9-fluoro-11,21-dihydroxy-16-methyl-, (11β, 16α)-. It has the molecular formula C22H29FO4 and a molecular weight of 376.47. The CAS Registry Number is 382-67-2. The chemical structure is:

Desoximetasone is a white to off-white, odorless, crystalline powder and is soluble in alcohol, acetone, chloroform, and hot ethyl acetate; slightly soluble in ether and benzene; and insoluble in water, dilute aqueous acids and alkalis.

Each gram of Desoximetasone Cream USP, 0.05% contains 0.5 mg of desoximetasone in an emollient cream consisting of white petrolatum, purified water, isopropyl myristate, lanolin alcohols, mineral oil, cetostearyl alcohol and edetate disodium.

Each gram of Desoximetasone Cream USP, 0.25% contains 2.5 mg of desoximetasone in an emollient cream consisting of white petrolatum, purified water, isopropyl myristate, lanolin alcohols, mineral oil and cetostearyl alcohol.

Each gram of Desoximetasone Gel USP, 0.05% contains 0.5 mg of desoximetasone in a gel base consisting of purified water, docusate sodium, edetate disodium, isopropyl myristate, carbomer 940, trolamine, and SDAG-3 95% alcohol.

CLINICAL PHARMACOLOGY

The corticosteroids are a class of compounds comprising steroid hormones secreted by the adrenal cortex and their synthetic analogs. In pharmacologic doses, corticosteroids are used primarily for their anti-inflammatory and/or immunosuppressive effects.

Topical corticosteroids, such as desoximetasone, are effective in the treatment of corticosteroid-responsive dermatoses primarily because of their anti-inflammatory, antipruritic, and vasoconstrictive actions. However, while the physiologic, pharmacologic, and clinical effects of the corticosteroids are well known, the exact mechanisms of their actions in each disease are uncertain. Desoximetasone, a corticosteroid, has been shown to have topical (dermatologic) and systemic pharmacologic and metabolic effects characteristic of this class of drugs.

Pharmacokinetics

The extent of percutaneous absorption of topical corticosteroids is determined by many factors including the vehicle and the integrity of the epidermal barrier, and the use of occlusive dressings.

Topical corticosteroids can be absorbed through normal intact skin. Inflammation and/or other disease processes in the skin may increase percutaneous absorption. Occlusive dressings substantially increase the percutaneous absorption of topical corticosteroids.

Once absorbed through the skin, topical corticosteroids enter pharmacokinetic pathways similar to systemically administered corticosteroids. Corticosteroids are bound to plasma proteins in varying degrees, are metabolized primarily in the liver and excreted by the kidneys. Some of the topical corticosteroids and their metabolites are also excreted into the bile.

Pharmacokinetic studies in men with Desoximetasone Cream USP, 0.25% with tagged desoximetasone showed a total of 5.2% ± 2.9% excretion in urine (4.1% ± 2.3%) and feces (1.1% ± 0.6%) and no detectable level (limit of sensitivity: 0.005 µg/mL) in the blood when it was applied topically on the back followed by occlusion for 24 hours. Seven days after application, no further radioactivity was detected in urine or feces. The half-life of the material was 15 ± 2 hours (for urine) and 17 ± 2 hours (for feces) between the third and fifth trial day. Studies with other similarly structured steroids have shown that predominant metabolite reaction occurs through conjugation to form the glucuronide and sulfate ester. Studies performed with Desoximetasone Cream USP, 0.05%; Desoximetasone Cream USP, 0.25% and Desoximetasone Gel USP, 0.05% indicate that they are in the high range of potency as compared with other topical corticosteroids.

INDICATIONS AND USAGE

Topical corticosteroids are high potency corticosteroids indicated for the relief of the inflammatory and pruritic manifestations of corticosteroid responsive dermatoses.

CONTRAINDICATIONS

Topical corticosteroids are contraindicated in those patients with a history of hypersensitivity to any of the components of the preparation.

WARNINGS

Desoximetasone Cream USP, 0.05%; Desoximetasone Cream USP, 0.25% and Desoximetasone Gel USP, 0.05% are not for ophthalmic use.

Keep out of reach of children.

PRECAUTIONS

General

Systemic absorption of topical corticosteroids can produce reversible hypothalamic-pituitary-adrenal (HPA) axis suppression with the potential for glucocorticosteroid insufficiency after withdrawal of treatment. Manifestations of Cushing's syndrome, hyperglycemia, and glucosuria can also be produced in some patients by systemic absorption of topical corticosteroids while on treatment. Use of more than one corticosteroid-containing product at the same time may increase total systemic glucocorticoid exposure. (See DOSAGE AND ADMINISTRATION section.)

Patients applying a topical steroid to a large surface area or to areas under occlusion should be evaluated periodically for evidence of HPA axis suppression. This may be done by using ACTH stimulation and urinary free cortisol tests.

If HPA axis suppression is noted, an attempt should be made to withdraw the drug, to reduce the frequency of application, or to substitute a less potent corticosteroid. Recovery of HPA axis function is generally prompt upon discontinuation of topical corticosteroids. Infrequently, signs and symptoms of glucocorticosteroid insufficiency may occur requiring supplemental systemic corticosteroids. For information on systemic supplementation, see prescribing information for those products.

Pediatric patients may be more susceptible to systemic toxicity from equivalent doses due to their larger skin surface to body mass ratios. (See PRECAUTIONS – Pediatric Use.)

If irritation develops, Desoximetasone Cream USP, 0.05%; Desoximetasone Cream USP, 0.25% or Desoximetasone Gel USP, 0.05% should be discontinued and appropriate therapy instituted. Allergic contact dermatitis with corticosteroids is usually diagnosed by observing failure to heal rather than noting a clinical exacerbation as with most topical products not containing corticosteroids. Such an observation should be corroborated with appropriate diagnostic patch testing.

If concomitant skin infections are present or develop, an appropriate antifungal or antibacterial agent should be used. If a favorable response does not occur promptly, use of Desoximetasone Cream USP, 0.05%; Desoximetasone Cream USP, 0.25% or Desoximetasone Gel USP, 0.05% should be discontinued until the infection has been adequately controlled.

This medication should not be used on the face, underarm or groin area.

As with other corticosteroids, therapy should be discontinued when control is achieved. If no improvement is seen within two weeks, the diagnosis and therapy should be re-evaluated.

Information for the Patient

Patients using topical corticosteroids should receive the following information and instructions. This information is intended to aid in the safe and effective use of this medication. It is not a disclosure of all possible adverse or unintended effects:

1. This medication is to be used as directed by the physician. It is for external use only. Avoid contact with the eyes.
2. This medication should not be used for any disorder other than that for which it was prescribed.
3. The treated skin area should not be bandaged, otherwise covered or wrapped, so as to be occlusive unless directed by the physician.
4. Patients should report to their physician any signs of local adverse reactions.
5. Other topical corticosteroid-containing products should not be used with Desoximetasone Cream USP, 0.05% or Desoximetasone Cream USP, 0.25% or Desoximetasone Gel USP, 0.05% without first talking to your physician.
6. If no improvement is seen in 2 weeks, contact your physician.

Laboratory Tests

The following tests may be helpful in evaluating patients for HPA axis suppression:

ACTH stimulation test
Urinary free cortisol test

Carcinogenesis, Mutagenesis, and Impairment of Fertility

Long-term animal studies have not been performed to evaluate the carcinogenic potential or the effect on fertility of desoximetasone.

Desoximetasone was nonmutagenic in the Ames test.

Pregnancy

Teratogenic Effects

Pregnancy Category C

Corticosteroids have been shown to be teratogenic in laboratory animals when administered systemically at relatively low dosage levels. Some corticosteroids have been shown to be teratogenic after dermal application in laboratory animals.

Desoximetasone has been shown to be teratogenic and embryotoxic in mice, rats, and rabbits when given by subcutaneous or dermal routes of administration in doses 3 to 30 times the human dose of Desoximetasone Cream USP, 0.25% or in doses 15 to 150 times the human dose of Desoximetasone Cream USP, 0.05% or Desoximetasone Gel USP, 0.05%.

There are no adequate and well-controlled studies in pregnant women. Desoximetasone Cream USP, 0.05%; Desoximetasone Cream USP, 0.25% and Desoximetasone Gel USP, 0.05% should be used during pregnancy only if the potential benefit justifies the potential risk to the fetus.

Nursing Mothers

It is not known whether topical administration of corticosteroids can result in sufficient systemic absorption to produce detectable quantities in breast milk. Systemically administered corticosteroids are secreted into breast milk in quantities not likely to have a deleterious effect on the infant. Nevertheless, a decision should be made whether to discontinue nursing or to discontinue the drug, taking into account the importance of the drug to the mother.

Pediatric Use

Pediatric patients may demonstrate greater susceptibility to topical corticosteroid-induced HPA axis suppression and Cushing's syndrome than adult patients because of a larger skin surface area to body weight ratio.

Hypothalamic-pituitary-adrenal (HPA) axis suppression, Cushing's syndrome and intracranial hypertension have been reported in pediatric patients receiving topical corticosteroids. Manifestations of adrenal suppression in pediatric patients include linear growth retardation, delayed weight gain, low plasma cortisol levels, and absence of response to ACTH stimulation. Manifestations of intracranial hypertension include bulging fontanelles, headaches, and bilateral papilledema. Chronic corticosteroid therapy may interfere with linear bone growth in pediatric patients.

Geriatric Use

Clinical studies of Desoximetasone Cream USP, 0.05%; Desoximetasone Cream USP, 0.25% and Desoximetasone Gel USP, 0.05% did not include sufficient numbers of subjects aged 65 and over to determine whether they respond differently from younger subjects. Other reported clinical experience has not identified differences in responses between the elderly and younger patients. In generally, dose selection for an elderly patient should be cautious.

ADVERSE REACTIONS

In controlled clinical studies the incidence of adverse reactions was low (0.8%) for Desoximetasone Cream USP, 0.05% and included pruritus, erythema, vesiculation and burning sensation. The incidence of adverse reactions was also 0.8% for Desoximetasone Cream USP, 0.25% and included burning, folliculitis, and folliculopustular lesions. The incidence of adverse reactions for Desoximetasone Gel USP, 0.05% was 0.3% with one subject reporting stinging and burning at the site of application.

The following local adverse reactions are reported infrequently when topical corticosteroids are used as recommended but may occur more frequently with the use of occlusive dressings and higher potency corticosteroids. These are listed in an approximate decreasing order of occurrence: burning, itching, irritation, dryness, folliculitis, hypertrichosis, acneiform eruptions, hypopigmentation, perioral dermatitis, allergic contact dermatitis, maceration of the skin, secondary infection, skin atrophy, striae, and miliaria.

Systemic absorption of topical corticosteroids has produced hypothalamic-pituitary-adrenal (HPA) axis suppression, manifestations of Cushing's syndrome, hyperglycemia, and glucosuria in some patients.

OVERDOSAGE

Topically applied Desoximetasone Cream USP, 0.05%; Desoximetasone Cream USP, 0.25% and Desoximetasone Gel USP, 0.05% can be absorbed in sufficient amounts to produce systemic effects (see PRECAUTIONS).

DOSAGE AND ADMINISTRATION

Apply a thin film of Desoximetasone Cream USP, 0.05% or Desoximetasone Cream USP, 0.25% or Desoximetasone Gel USP, 0.05% to the affected skin areas twice daily. Rub in gently.

HOW SUPPLIED

Desoximetasone Cream USP, 0.05% is supplied in 15 gram (NDC 51672-1271-1), 60 gram (NDC 51672-1271-3), 100 gram (NDC 51672-1271-7) tubes and 300 gram carton (3 × 100 gram tubes) (NDC 51672-1271-8).

Desoximetasone Cream USP, 0.25% is supplied in 15 gram (NDC 51672-1270-1), 60 gram (NDC 51672-1270-3), 100 gram (NDC 51672-1270-7) tubes and 200 gram carton (2 × 100 gram tubes) (NDC 51672-1270-9)

Desoximetasone Gel USP, 0.05% is supplied in 15 gram (NDC 51672-1261-1) and 60 gram (NDC 51672-1261-3) tubes.

STORAGE AND HANDLING

Store at 20° - 25°C (68° - 77°F) [see USP Controlled Room Temperature].

Mfd. by: Taro Pharmaceuticals Inc., Brampton, Ontario, Canada L6T 1C1
Revised June, 2009

PK-6352-0

PRINCIPAL DISPLAY PANEL - 0.05%, 15 g Tube Carton

NDC 51672-1271-1

15 g

Desoximetasone
Cream USP, 0.05%

FOR EXTERNAL USE ONLY.
NOT FOR OPHTHALMIC USE.

Rx only

Keep this and all medications out of the reach of children.

TARO

PRINCIPAL DISPLAY PANEL - 0.25%, 15 g Tube Carton

NDC 51672-1270-1

15 g

Desoximetasone
Cream USP, 0.25%

FOR EXTERNAL USE ONLY.
NOT FOR OPHTHALMIC USE.

Rx only

Keep this and all medications out of the reach of children.

TARO

PRINCIPAL DISPLAY PANEL - 0.05%, 15 g Tube Carton

NDC 51672-1261-1

15 g

Desoximetasone
Gel USP, 0.05%

FOR EXTERNAL USE ONLY.
NOT FOR OPHTHALMIC USE.

Rx only

Keep this and all medications out of the reach of children.

TARO